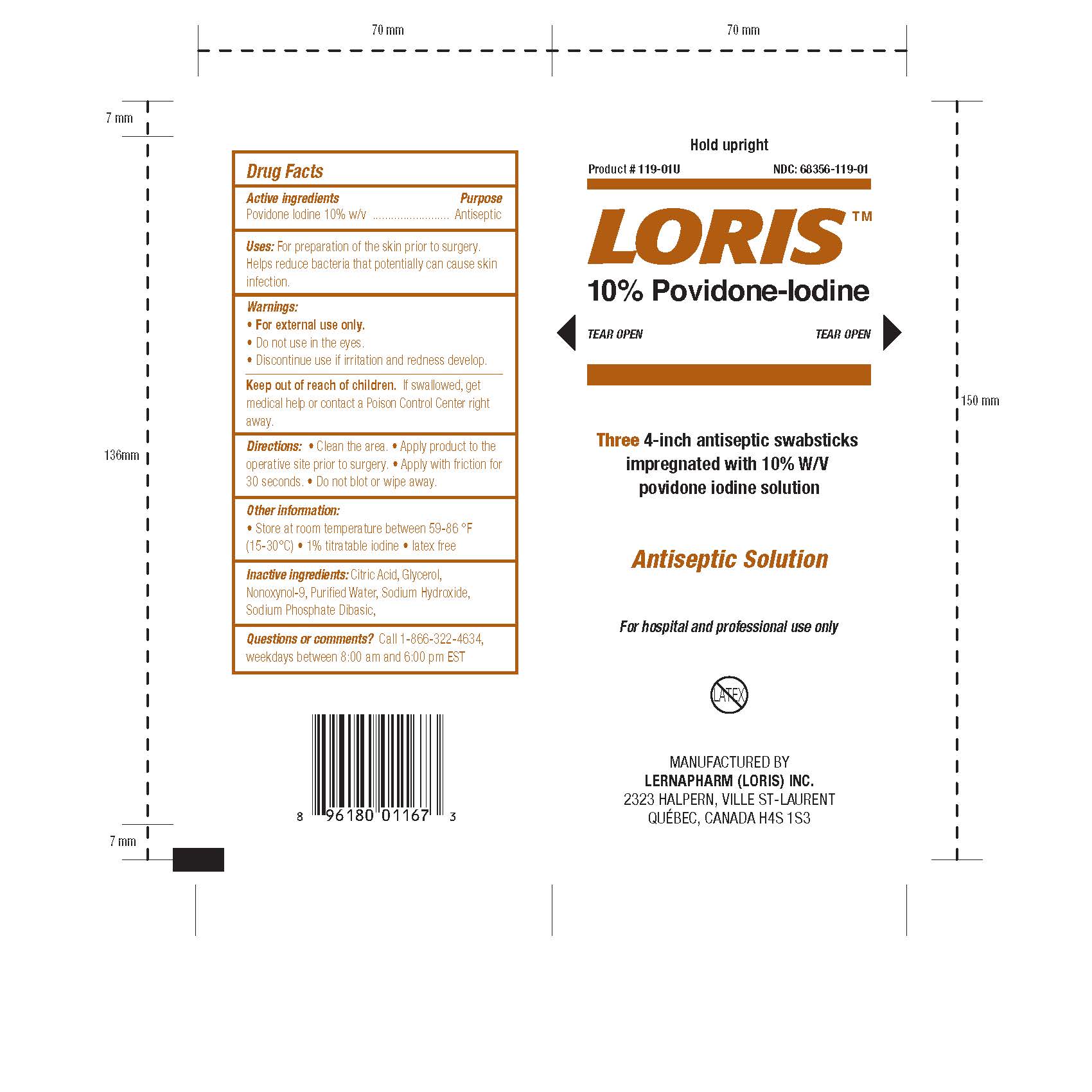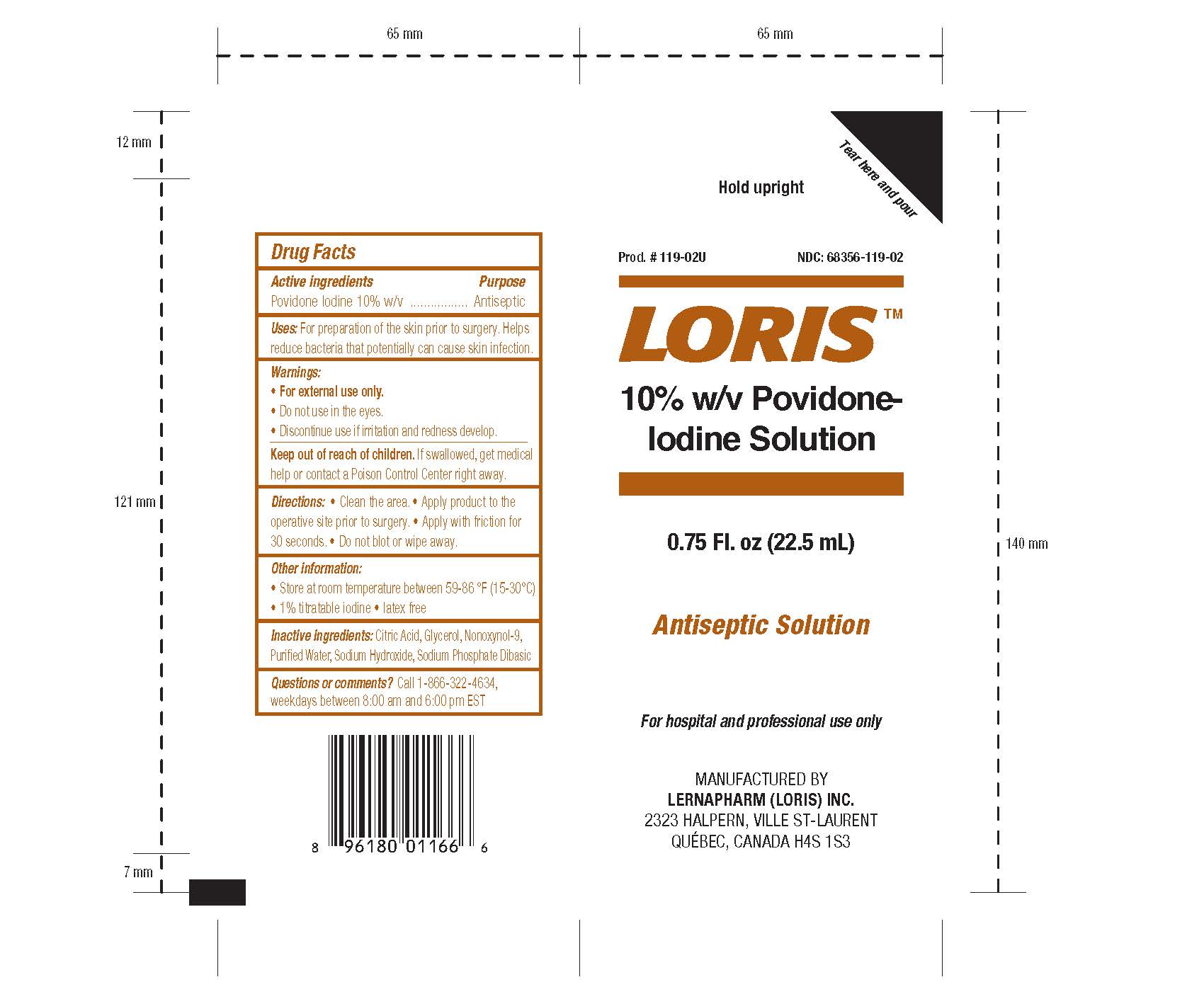 DRUG LABEL: Loris Povidone-Iodine
NDC: 68356-119 | Form: LIQUID
Manufacturer: LernaPharm Loris Inc.
Category: otc | Type: HUMAN OTC DRUG LABEL
Date: 20231021

ACTIVE INGREDIENTS: POVIDONE-IODINE 1 g/100 mL
INACTIVE INGREDIENTS: SODIUM PHOSPHATE, DIBASIC; ANHYDROUS CITRIC ACID; GLYCERIN; NONOXYNOL-9; WATER; SODIUM HYDROXIDE

Drug Facts

Active Ingredients

Povidone Iodine 10% w/v

Purpose

Antiseptic

Uses

For preparation of the skin prior to surgery. Helps reduce bacteria that potentially can cause skin infection.

Warnings

For External Use Only

- Do not use in the eyes.
- Discontinue use if irritation and redness develop.

Keep out of reach of children. If swallowed, get medical help or contact a Poison Control Center right away.

Directions

- Clean the area.
- Apply product to the operative site prior to surgery.
- Apply with friction for 30 seconds.
- Do not blot or wipe away.

Other Information

Store at room temperature between 59-86oF (15-30oC). 1% titratable iodine. Latex free

Inactive Ingredients

Citric Acid, Glycerol, Nonoxynol-9, Purified Water, Sodium Hydroxide, Sodium Phosphate Dibasic

Questions or comments?

Call 1-866-322-4634, weekdays between 8:00 am and 6:00 pm EST

Principal Display Panel

Hold upright

Product # 119-XXU NDC: 68356-119-XX

Loris Povidone-Iodine [Solution]

[TEAR OPEN] [Tear here and pour]

[Three 4-inch antiseptic swabsticks impregnated with 10% W/V povidone iodine solution]

[0.75 Fl. oz (22.5 mL)]

Antiseptic Solution

For hospital and professional use only

MANUFACTURED BY

LERNAPHARM (LORIS) INC.

2323 HALPERN, VILLE ST-LAURENT

QUEBEC, CANADA H4S 1S3